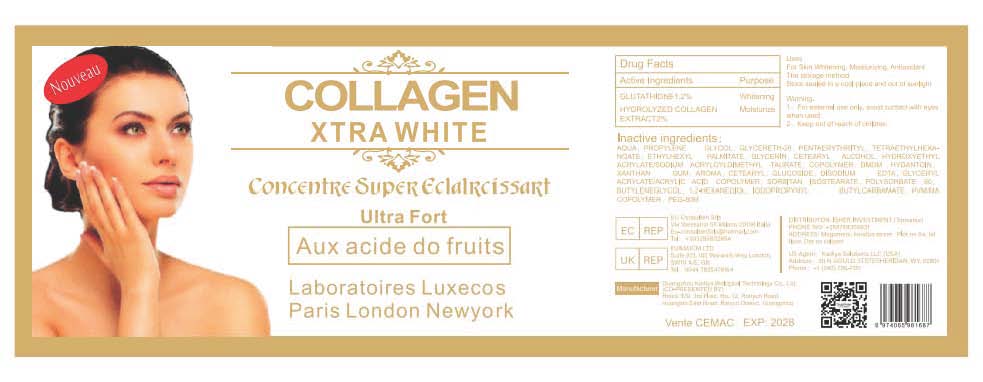 DRUG LABEL: COLLAGEN XTRA WHITE SERUM
NDC: 84423-076 | Form: SOLUTION, CONCENTRATE
Manufacturer: Guangzhou Kadiya Biotechnology Co., Ltd.
Category: otc | Type: HUMAN OTC DRUG LABEL
Date: 20250218

ACTIVE INGREDIENTS: GLUTATHIONE 1.2 g/100 mL
INACTIVE INGREDIENTS: GLYCERYL ACRYLATE/ACRYLIC ACID COPOLYMER (300000 CP AT 2%); PENTAERYTHRITYL TETRAETHYLHEXANOATE; PEG-90M; CETEARYL ALCOHOL; HYDROXYETHYL ACRYLATE/SODIUM ACRYLOYLDIMETHYL TAURATE COPOLYMER (45000 MPA.S AT 1%); XANTHAN GUM; IODOPROPYNYL BUTYLCARBAMATE; GLYCERETH-26; GLYCERIN; CETEARYL GLUCOSIDE; PROPYLENE GLYCOL; POLYSORBATE 60; 1,3-BUTYLENEGLYCOL DIMETHACRYLATE; AQUA; ETHYLHEXYL PALMITATE; DMDM HYDANTOIN; EDETATE DISODIUM; SORBITAN ISOSTEARATE; 1,2-HEXANEDIOL; METHYL VINYL ETHER AND MALEIC ANHYDRIDE COPOLYMER (1100000 WAMW)

PURPOSE

For Skin Whitening, Moisturizing, Antioxidant

INACTIVE INGREDIENT

AQUA，PROPYLENE GLYCOL，GLYCERETH-26，PENTAERYTHRITYL，TETRAETHYLHEXANOATE，ETHYLHEXYL PALMITATE，GLYCERIN，CETEARYL ALCOHOL，HYDROXYETHYL ACRYLATE/SODIUM ACRYLOYLDIMETHYL TAURATE，COPOLYMER，DMDM HYDANTOIN，XANTHAN GUM，AROMA，CETEARYL，GLUCOSIDE，DISODIUM EDTA，GLYCERYL ACRYLATE/ACRYLIC ACID COPOLYMER，SORBITAN ISOSTEARATE，POLYSORBATE 60，BUTYLENEGLYCOL，1,2-HEXANEDIOL，IODOPROPYNYL BUTYLCARBAMATE，PVM/MA COPOLYMER，PEG-90M

Warning.
1、For external use only, avoid contact with eyes when used
2、Keep out of reach of children

INDICATIONS AND USAGE

For Skin Whitening, Moisturizing, Antioxidant

DOSAGE AND ADMINISTRATION

Gently pat your face with your finger or fingertips to help the serum absorb better

KEEP OUT OF REACH OF CHILDREN SECTION

Active Ingredients
GLUTATHIONE1.2%
HYDROLYZED COLLAGEN EXTRACT2%

PACKAGE LABEL

Active Ingredients
GLUTATHIONE1.2%
HYDROLYZED COLLAGEN EXTRACT2%

Uses：
For Skin Whitening, Moisturizing, Antioxidant
The storage method：
Store sealed in a cool place and out of sunlight

Warning.
1、For external use only, avoid contact with eyes when used
2、Keep out of reach of children

Inactive ingredients：
AQUA，PROPYLENE GLYCOL，GLYCERETH-26，PENTAERYTHRITYL，TETRAETHYLHEXANOATE，ETHYLHEXYL PALMITATE，GLYCERIN，CETEARYL ALCOHOL，HYDROXYETHYL ACRYLATE/SODIUM ACRYLOYLDIMETHYL TAURATE，COPOLYMER，DMDM HYDANTOIN，XANTHAN GUM，AROMA，CETEARYL，GLUCOSIDE，DISODIUM EDTA，GLYCERYL ACRYLATE/ACRYLIC ACID COPOLYMER，SORBITAN ISOSTEARATE，POLYSORBATE 60，BUTYLENEGLYCOL，1,2-HEXANEDIOL，IODOPROPYNYL BUTYLCARBAMATE，PVM/MA COPOLYMER，PEG-90M